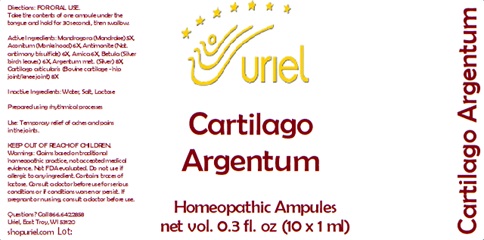 DRUG LABEL: Cartilago Argentum
NDC: 48951-3261 | Form: LIQUID
Manufacturer: Uriel Pharmacy Inc.
Category: homeopathic | Type: HUMAN OTC DRUG LABEL
Date: 20241126

ACTIVE INGREDIENTS: SILVER 8 [hp_X]/1 mL; MANDRAGORA OFFICINARUM ROOT 5 [hp_X]/1 mL; ACONITUM NAPELLUS 6 [hp_X]/1 mL; ANTIMONY TRISULFIDE 6 [hp_X]/1 mL; ARNICA MONTANA 6 [hp_X]/1 mL; BETULA PUBESCENS LEAF 6 [hp_X]/1 mL; BOS TAURUS CARTILAGE 8 [hp_X]/1 mL
INACTIVE INGREDIENTS: WATER; SODIUM CHLORIDE; LACTOSE

Cartilago Argentum

INDICATIONS AND USAGE

Directions: FOR ORAL USE.

DOSAGE AND ADMINISTRATION

Take the contents of one ampule under the tongue and hold for 30 seconds, then swallow.

ACTIVE INGREDIENT

Active Ingredients: Mandragora (Mandrake) 5X, Aconitum (Monkshood) 6X, Antimonite (Nat. antimony trisulfide) 6X, Arnica 6X, Betula (Silver birch leaves) 6X, Argentum met. (Silver) 8X, Cartilago articularis (Bovine cartilage - hip joint/knee joint) 8X

Inactive Ingredients: Water, Salt, Lactose

Prepared using rhythmical processes.

PURPOSE

Use: Temporary relief of aches and pains in the joints.

KEEP OUT OF REACH OF CHILDREN.

WARNINGS

Warnings: Claims based on traditional homeopathic practice, not accepted medical evidence. Not FDA evaluated. Do not use if allergic to any ingredient. Contains traces of lactose. Consult a doctor before use for serious conditions or if conditions worsen or persist. If pregnant or nursing, consult a doctor before use.

QUESTIONS

Questions? Call 866.642.2858 Uriel, East Troy, WI 53120 shopuriel.com